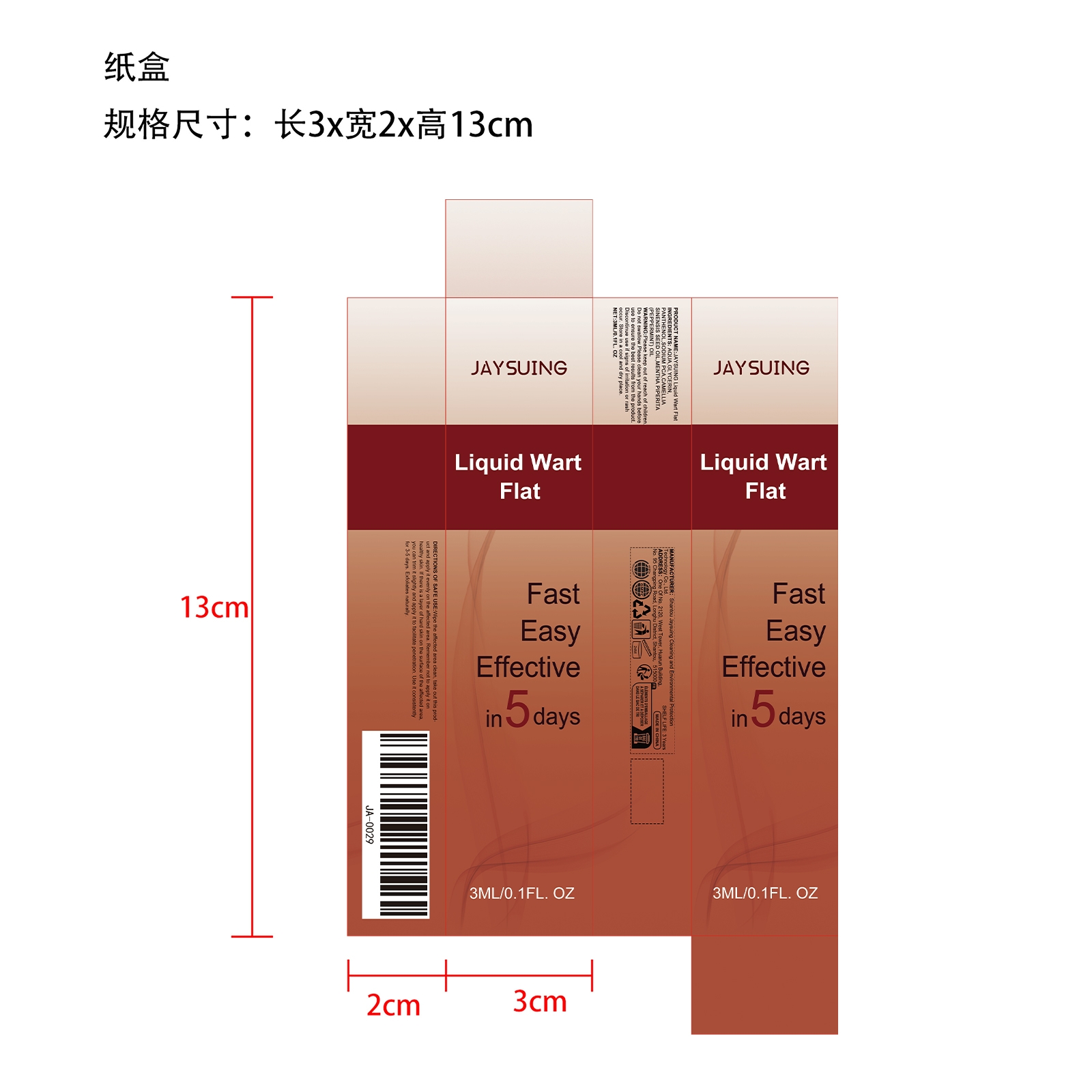 DRUG LABEL: JAYSUING Liquid Wart Flat
NDC: 85060-005 | Form: LIQUID
Manufacturer: Shantou Jaysuing Cleaning and Environmental Protection Technology Co., Ltd.
Category: otc | Type: HUMAN OTC DRUG LABEL
Date: 20251127

ACTIVE INGREDIENTS: CAMELLIA SINENSIS SEED OIL 0.0006 mg/3 mg
INACTIVE INGREDIENTS: AQUA 2.8038 mg/3 mg; GLYCERIN 0.12 mg/3 mg; SODIUM PCA 0.03 mg/3 mg; PANTHENOL 0.045 mg/3 mg; MENTHA PIPERITA (PEPPERMINT) OIL 0.0006 mg/3 mg

ACTIVE INGREDIENT

CAMELLIA SINENSIS SEED OIL、MENTHA PIPERITA (PEPPERMINT) OIL

WHEN USING

Wipe the affected area clean, take out this product and apply it evenly on the affected area. Remember not to apply it on healthy skin. If there is a layer of hard skin on the surface of the affected area, you can trim it slightly and apply it to facilitate penetration. Use it consistently for 3-5 days. Exfoliates naturally.

WARNINGS

Please keep out of reach of children. Do not swallow.Please clean your hands before use to ensure the best results from the product. Discontinue use if signs of irritation or rash occur. Store in a cool and dry place.

DO NOT USE

Discontinue use if signs of irritation or rash occur.

STOP USE

Discontinue use if signs of irritation or rash occur.

PURPOSE

Fast Easy Effective in 5 days

KEEP OUT OF REACH OF CHILDREN

Please keep out of reach of children. Do not swallow.

STORAGE AND HANDLING

Store in a cool and dry place.

INACTIVE INGREDIENT

AQUA、GLYCERIN、PANTHENOL、SODIUM PCA

DOSAGE AND ADMINISTRATION

Use it consistently for 3-5 days. Exfoliates naturally.

INDICATIONS AND USAGE

Wipe the affected area clean, take out this product and apply it evenly on the affected area. Remember not to apply it on healthy skin. If there is a layer of hard skin on the surface of the affected area, you can trim it slightly and apply it to facilitate penetration.